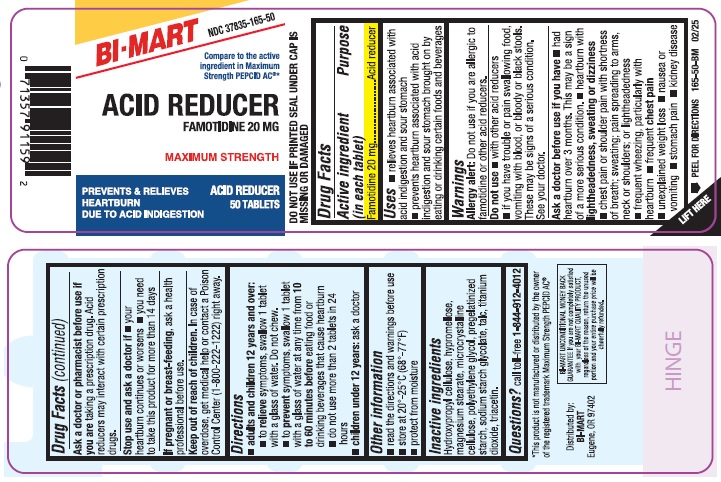 DRUG LABEL: Famotidine
NDC: 37835-165 | Form: TABLET
Manufacturer: Bi-Mart
Category: otc | Type: HUMAN OTC DRUG LABEL
Date: 20250601

ACTIVE INGREDIENTS: FAMOTIDINE 20 mg/1 1
INACTIVE INGREDIENTS: HYDROXYPROPYL CELLULOSE, UNSPECIFIED; HYPROMELLOSE, UNSPECIFIED; MAGNESIUM STEARATE; MICROCRYSTALLINE CELLULOSE; POLYETHYLENE GLYCOL, UNSPECIFIED; STARCH, CORN; SODIUM STARCH GLYCOLATE TYPE A; TALC; TITANIUM DIOXIDE; TRIACETIN

Drug Facts

Active ingredient (in each tablet)

Famotidine 20 mg

Purpose

Acid reducer

Uses

- relieves heartburn associated with acid indigestion and sour stomach
- prevents heartburn associated with acid indigestion and sour stomach brought on by eating or drinking certain food and beverages

Warnings

Allergy alert:

Do not use if you are allergic to famotidine or other acid reducers.

Do not use

- with other acid reducers
- if you have trouble or pain swallowing food, vomiting with blood, or bloody or black stools. These may be signs of a serious condition. See your doctor.

Ask a doctor before use if you have

- had heartburn over 3 months. This may be a sign of a more serious condition.
- heartburn with lightheadedness, sweating, or dizziness
- chest pain or shoulder pain with shortness of breath; sweating; pain spreading to arms, neck or shoulders; or lightheadedness
- frequent wheezing, particularly with heartburn
- frequent chest pain
- unexplained weight loss
- nausea or vomiting
- stomach pain
- kidney disease

Ask a doctor or pharmacist before use if you aretaking a prescription drug. Acid reducers may interact with certain prescription drugs.

Stop use and ask a doctor if

- your heartburn continues or worsens
- you need to take this product for more than 14 days

PREGNANCY OR BREAST FEEDING

If pregnant or breast-feeding, ask a health professional before use.

Keep out of reach of children. In case of overdose, get medical help or contact a Poison Control Center (1-800-222-1222) right away.

Directions

- adults and children 12 years and over:
  - to relieve symptoms, swallow 1 tablet with a glass of water. Do not chew.
  - to prevent symptoms, swallow 1 tablet with a glass of water at any time from 10 to 60 minutes before eating food or drinking beverages that cause heartburn
  - do not use more than 2 tablets in 24 hours
- children under 12 years: ask a doctor

Other information

- read the directions and warnings before use
- store at 20° - 25°C (68° - 77°F)
- protect from moisture

Inactive ingredients

Hydroxypropyl cellulose, hypromellose, magnesium stearate, microcrystalline cellulose, pregelatinized starch, sodium starch glycolate, polyethylene glycol, talc, titanium dioxide, triacetin.

Questions?

call toll-free 1-844-912-4012